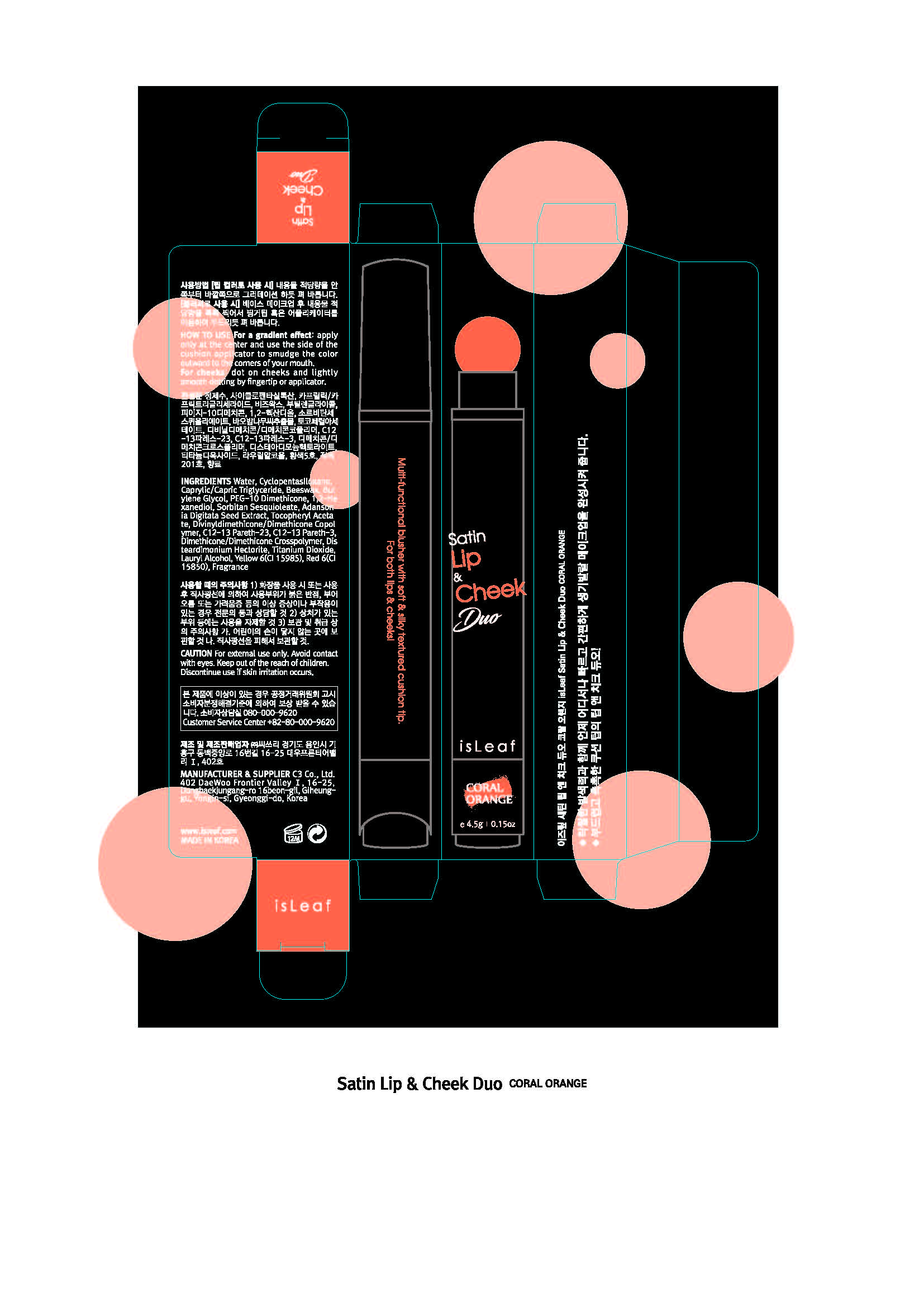 DRUG LABEL: isLeaf Satin Lip and Cheek Duo Coral Orange
NDC: 70818-005 | Form: LIQUID
Manufacturer: C3 Co., Ltd.
Category: otc | Type: HUMAN OTC DRUG LABEL
Date: 20170808

ACTIVE INGREDIENTS: DIMETHICONE 0.15 g/100 g
INACTIVE INGREDIENTS: WATER; LAURYL ALCOHOL; BUTYLENE GLYCOL

Drug Facts

ACTIVE INGREDIENT

dimethicone

INACTIVE INGREDIENT

wter butylene glycol, beeswax, etc

PURPOSE

for a gradient effect

keep out of reach of the children

INDICATIONS AND USAGE

For a gradient effect, apply only at the center and use the side of the cushion applicator to smudge the color outward to the corners of your mouth.

For cheeks, dot on cheeks and lightly smooth dotting by fingertip or applicator

WARNINGS

1. If the following symptoms occur after product use, stop using the product immediately and consult a dermatologist (continuous use can exacerbate the symptoms).
1) Occurrence of red spots, swelling, itchiness, and other skin irritation
2) If the symptoms above occur after the application area is exposed to direct sunlight
2. Do not use on open wounds, eczema, and other skin irritations
3. Precaution for Storage and Handling
1) Close the lid after use
2) Keep out of reach of infants and children
3) Do not to store in a place with high/low temperature and exposed to direct sunlight

4. Use as avoiding eye areas.

DOSAGE AND ADMINISTRATION

for external use only